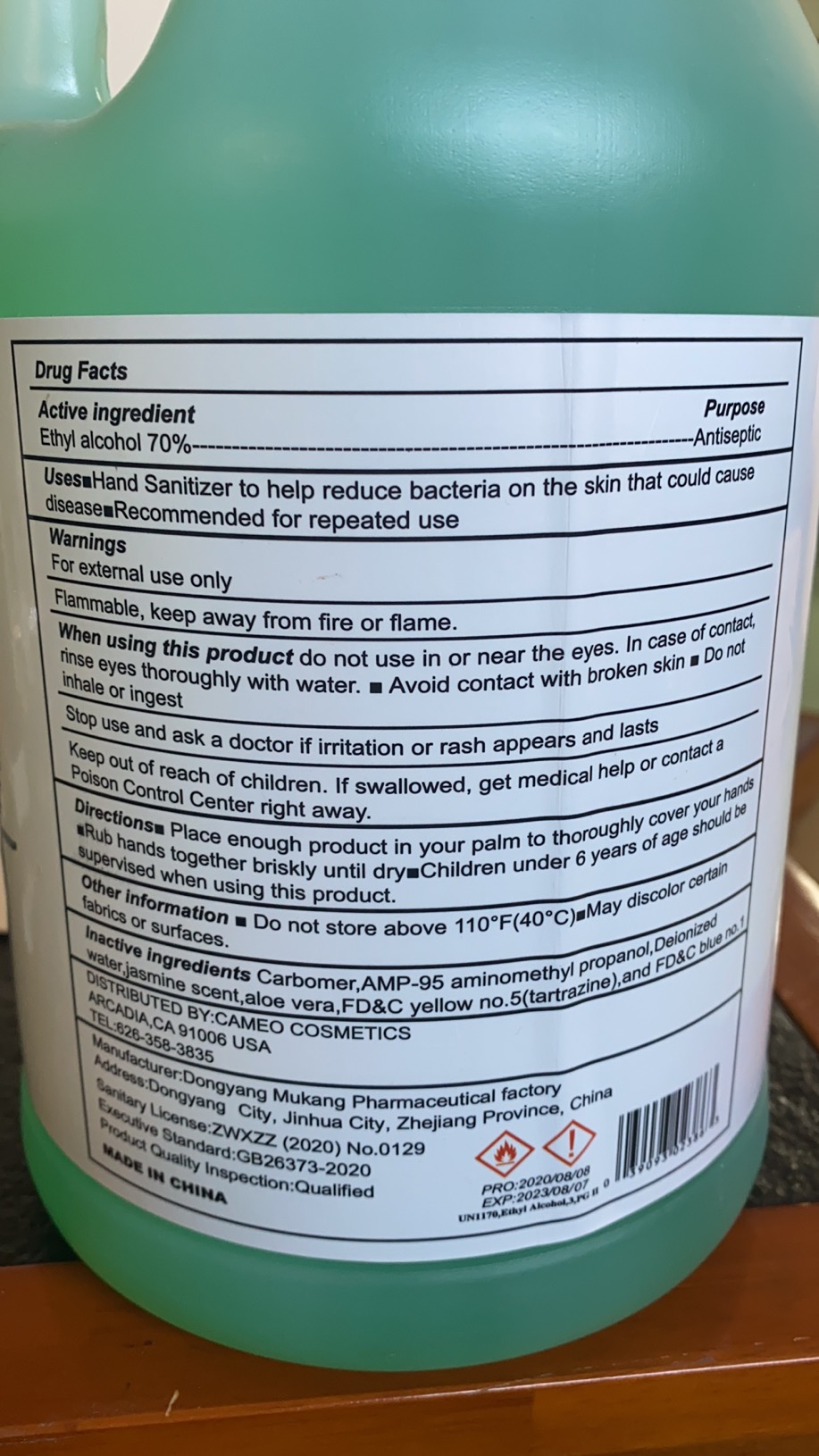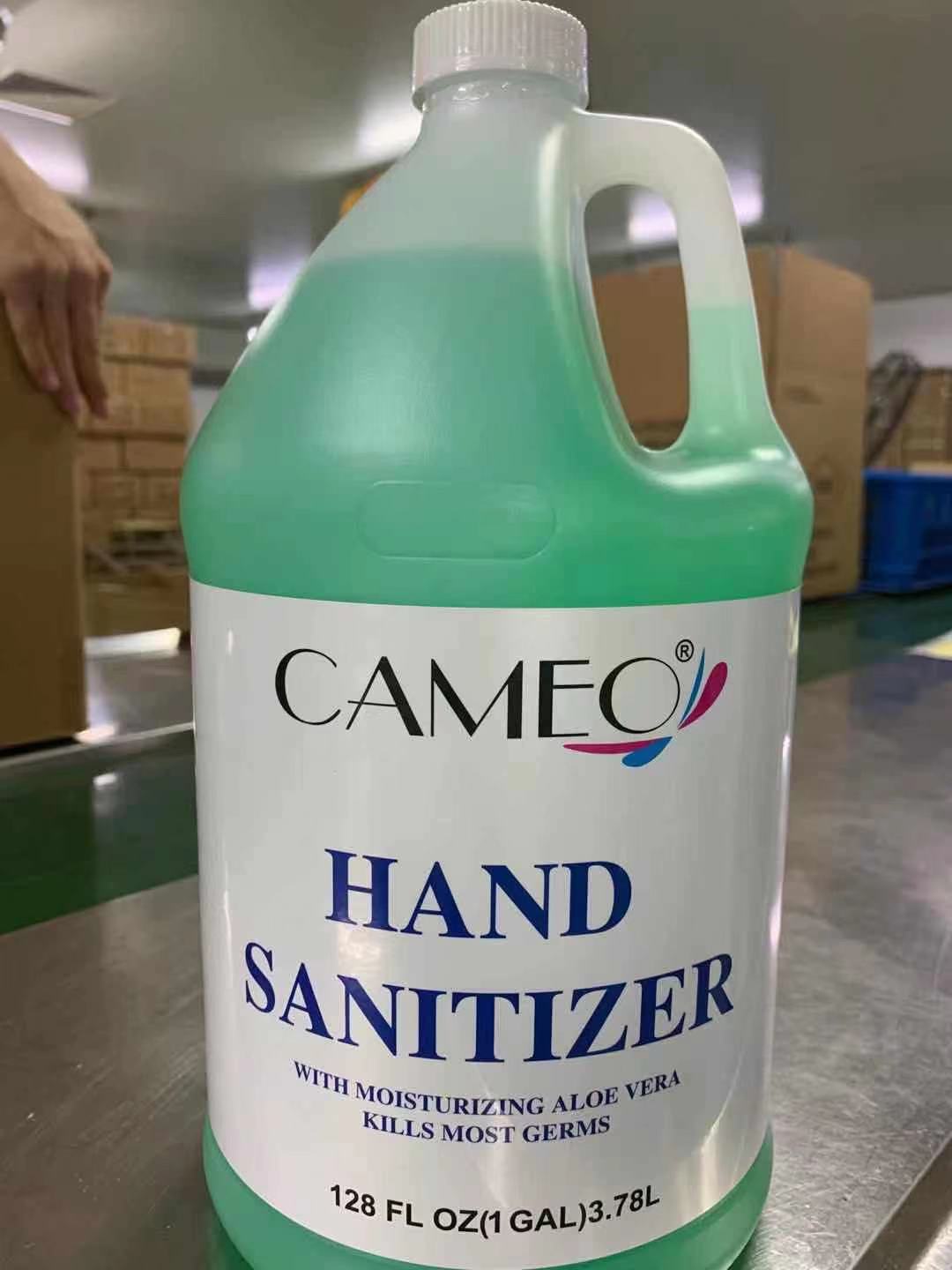 DRUG LABEL: Hand Sanitizer
NDC: 75586-010 | Form: GEL
Manufacturer: Dongyang Mukang Pharmaceutical Factory	
Category: otc | Type: HUMAN OTC DRUG LABEL
Date: 20201113

ACTIVE INGREDIENTS: ALCOHOL 70 mL/100 mL
INACTIVE INGREDIENTS: ALOE VERA LEAF; FD&C BLUE NO. 1; FD&C YELLOW NO. 5; AMINOMETHYLPROPANOL; JASMINUM OFFICINALE LEAF; WATER; CARBOMER COPOLYMER TYPE A

75586-010-01 3780ml

Active Ingredient(s)

Alcohol 70% v/v. Purpose: Antiseptic

Purpose

Antiseptic, Hand Sanitizer

Use

Hand Sanitizer to help reduce bacteria on the skin that could cause disease.

Recommended for repeated use.

Warnings

For external use only. Flammable. Keep away from heat or flame

Do not use

- in children less than 2 months of age
- on open skin wounds

When using this product do not use in or near the eyes. In case of contact , rinse eyes thoroughly with water.

- Avoid contact with broken skin
- Do not inhale or ingest.

Stop use and ask a doctor if irritation or rash oppears and lasts.

Keep out of reach of children. If swallowed, get medical help or contact a Poison Control Center right away.

Directions

- Place enough product in your palm to thoroughly cover your hands
- Rub hands together briskly until dry
- Children under 6 years of ages should be supervised when using this product.

Other information

- Do not store above 110℉（40℃）
- May discolor certain fabrics or surfaces

Inactive ingredients

Water, Carbomer, AMP-95 aminomethly propanol, jasmine scent, aloe vera, FD&C yellow no.5(tartrazine), and FD&C blue no.1